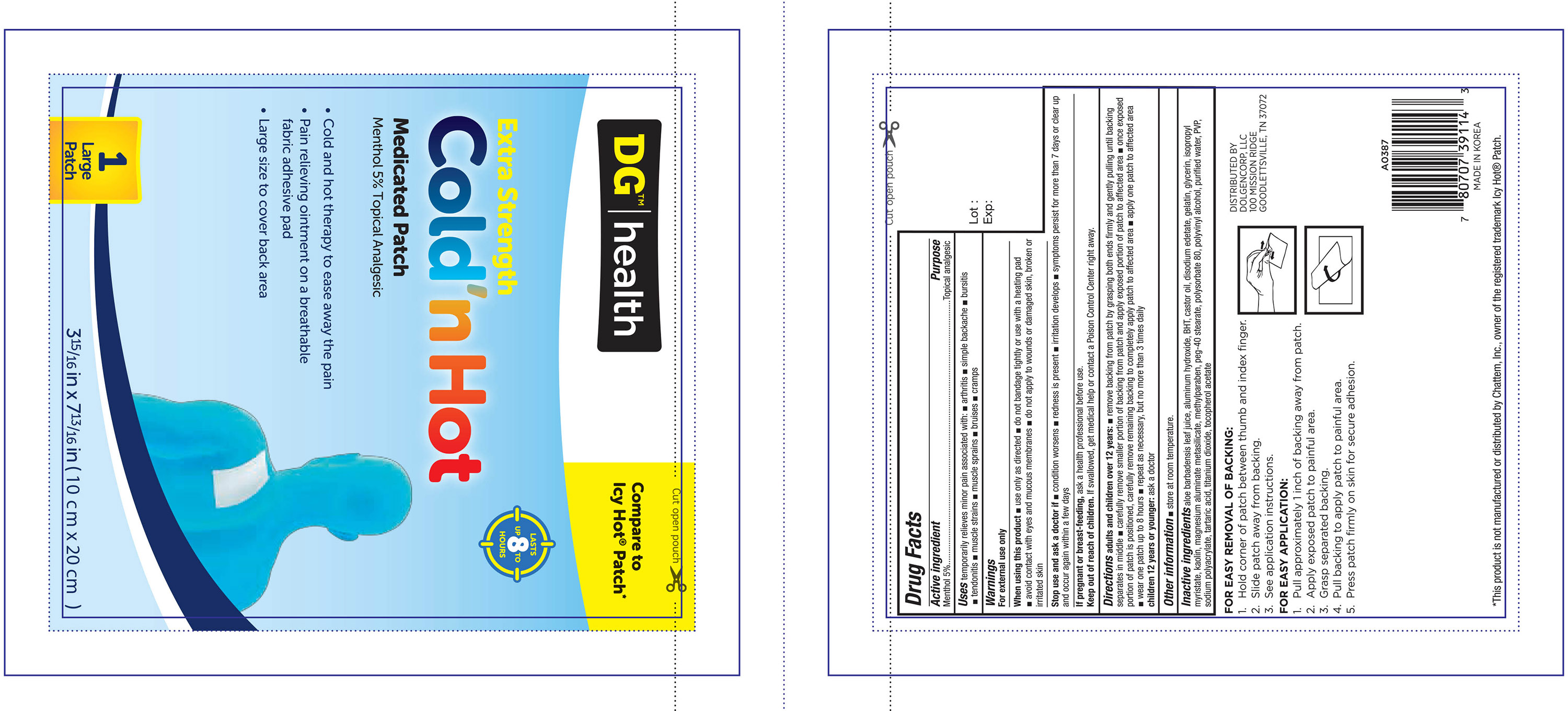 DRUG LABEL: DG Health Extra Strength Medicated
NDC: 55910-395 | Form: PATCH
Manufacturer: Dolgencorp Inc
Category: otc | Type: HUMAN OTC DRUG LABEL
Date: 20160601

ACTIVE INGREDIENTS: MENTHOL 750 mg/1 1
INACTIVE INGREDIENTS: ALOE VERA LEAF; ALUMINUM HYDROXIDE; BUTYLATED HYDROXYTOLUENE; CASTOR OIL; EDETATE DISODIUM; GELATIN; GLYCERIN; ISOPROPYL MYRISTATE; KAOLIN; SILODRATE; METHYLPARABEN; PEG-40 STEARATE; POLYSORBATE 80; POLYVINYL ALCOHOL, UNSPECIFIED; WATER; POVIDONES; SODIUM POLYACRYLATE (8000 MW); TARTARIC ACID; TITANIUM DIOXIDE; ALPHA-TOCOPHEROL ACETATE

Active ingredient Purpose

Menthol 5%............................................................Topical Analgesic

Uses

temporarily relieves minor pain associated with:

- arthritis
- simple backache
- bursitis
- tendonitis
- muscle strains
- muscle sprains
- bruises
- cramps

Warnings

For external use only

When using this product

- Use only as directed
- do not bandage tightly or use with a heating pad
- avoid contact with eyes and mucous membranes
- do not apply to wounds or damaged skin, broken or irritated skin

Stop use and ask a doctor if:

- condition worsens
- redness is present
- irritation develops
- symptoms persist for more than 7 days or clear up and occur again within a few days

PREGNANCY OR BREAST FEEDING

If pregnant or breast-feeding, ask a health professional before use.

Keep out of reach of children. If swallowed, get medical help or contact a Poison Control Center right away.

INDICATIONS AND USAGE

Directions adults and children over 12 years:

- remove backing from patch by grasping both ends firmly and gently pulling until backing separates in middle
- carefully remove smaller portion of backing from patch and apply exposed portion of patch to affected area
- once exposed portion of patch is positioned, carefully remove remaining backing to completely apply patch to affected area
- apply one patch to affected area
- wear one patch up to 8 hours
- repeat as necessary, but no more than 3 times daily

Children 12 years or younger: ask a doctor

Other information

- store at room temperature

Inactive ingredients

aloe barbadensis leaf juice, aluminum hydroxide, BHT, castor oil, disodium edetate, gelatin, glycerin, isopropyl myristate, kaolin, magnesium

aluminate metasilicate, methylparaben, peg-40 stearate, polysorbate 80, polyvinyl alcohol, purified water, PVP, sodium polyacrylate, tartaric

acid, titanium dioxide, tocopherol acetate

DOSAGE AND ADMINISTRATION

Distributed By:

Dolgencorp. LLC

100 Mission Ridge

Goodlettsville, TN 37072

Made in Korea